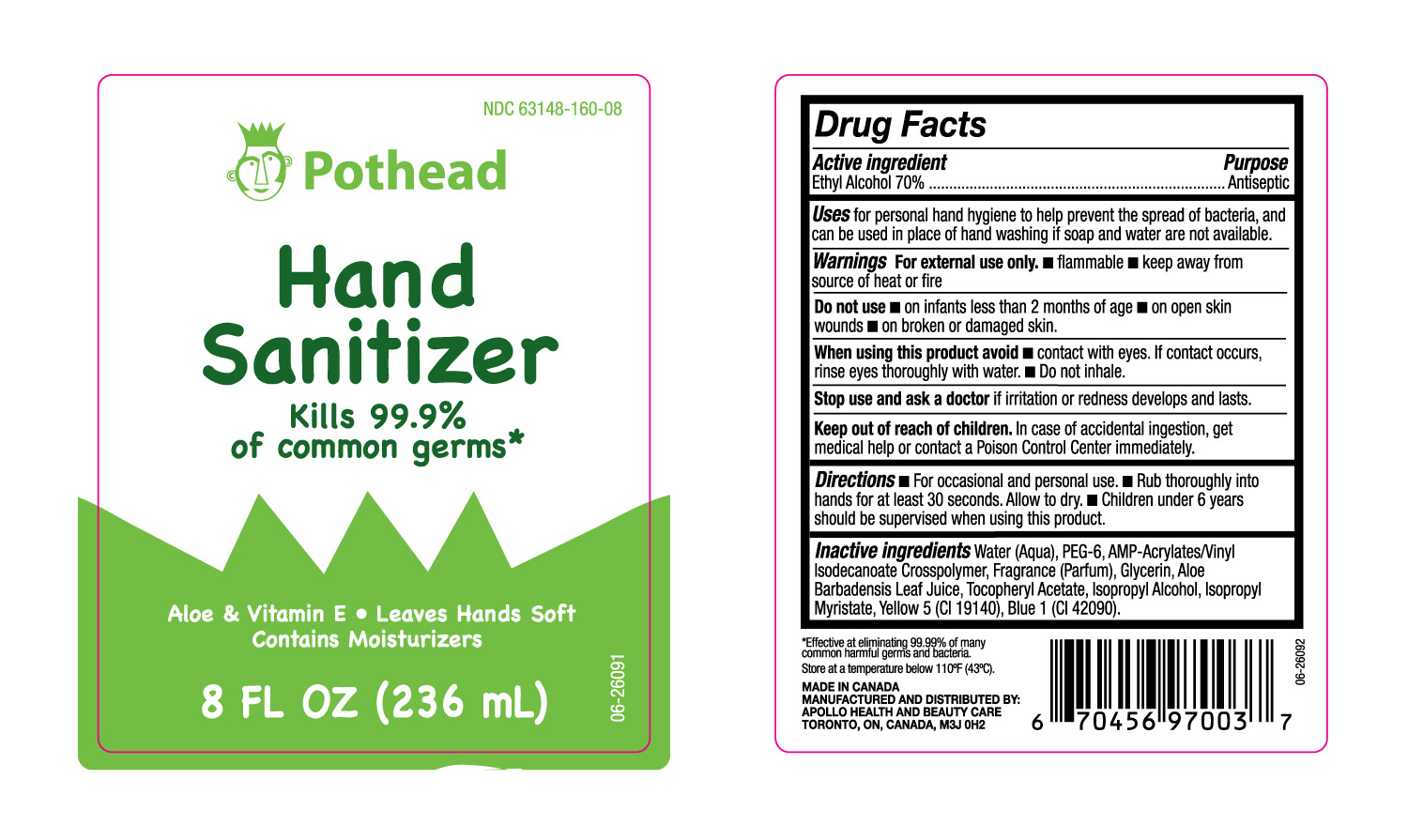 DRUG LABEL: Ethyl Alcohol
NDC: 63148-160 | Form: GEL
Manufacturer: Apollo Health and Beauty Care
Category: otc | Type: HUMAN OTC DRUG LABEL
Date: 20240403

ACTIVE INGREDIENTS: ALCOHOL 70 mL/100 mL
INACTIVE INGREDIENTS: ACRYLATES/VINYL ISODECANOATE CROSSPOLYMER (10000 MPA.S NEUTRALIZED AT 0.5%); .ALPHA.-TOCOPHEROL ACETATE; POLYETHYLENE GLYCOL 300; BASIC YELLOW 5; GLYCERIN; ISOPROPYL ALCOHOL; DIRECT BLUE 1; ISOPROPYL MYRISTATE; FRAGRANCE CLEAN ORC0600327; ALOE VERA LEAF

Pot Head Hand Sanitizer 63148-160-08

Active Ingredent

Ethanol (70%)

Purpose

Antiseptic

Uses

For Personal hand hygiene to help the spread of bacteria, and can be used in place of hand washing if soap and water are not available.

Warnings

For external use only

- Flammable
- Keep away from source of heat or fire.

Do not use

- on infants less than 2 months of age.
- on open skin wounds.
- on broken or damaged skin.

When using this product avoid

- Contact with eyes. If contact occurs, rinse eyes thoroughly with water.
- Do not inhale.

Stop use and ask a doctor

if irritation or redness develops and lasts.

Keep out of reach of children.

In case of accidental ingestion, get medical help or contact a Poison Control Center immediately.

Directions

- For occasional and personal use.
- Rub thoroughly into hands for at least 30 seconds. Allow to dry.
- Children under 6 years should be supervised when using thiis product.

Inactive Ingredients

Water (Aqua), PEG-6, AMP-Acrylates/Vinyl Isodecanoate Crosspolymer, Fragrance (Parfum), Glycerin, Aloe Barbadensis Leaf Juice, Tocopheryl Acetate, Isopropyl Alcohol, Isopropyl Myristate, Yellow 5 (CI 19140), Blue 1 (CI 42090).